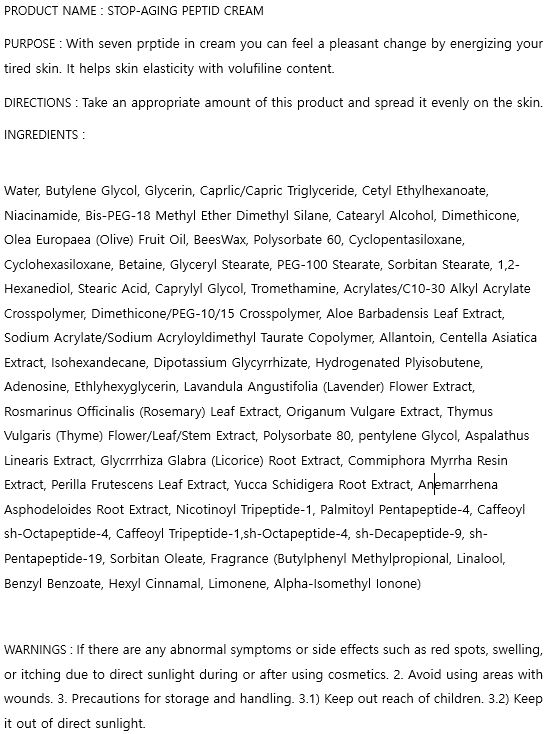 DRUG LABEL: STOP-AGING PEPTIDE
NDC: 74997-0005 | Form: CREAM
Manufacturer: J&J COMPANY
Category: otc | Type: HUMAN OTC DRUG LABEL
Date: 20200812

ACTIVE INGREDIENTS: NIACINAMIDE 2 g/100 mL; ADENOSINE 0.04 g/100 mL
INACTIVE INGREDIENTS: GLYCERIN; BUTYLENE GLYCOL; WATER

J&J COMPANY - STOP-AGING PEPTIDE EYE CREAM

ACTIVE INGREDIENT

Niacinamide, Adenosine

INACTIVE INGREDIENT

Water, Butylene Glycol, Glycerin, Caprlic/Capric Triglyceride, Cetyl Ethylhexanoate, Niacinamide, Bis-PEG-18 Methyl Ether Dimethyl Silane, Catearyl Alcohol, Dimethicone, Olea Europaea (Olive) Fruit Oil, BeesWax, Polysorbate 60, Cyclopentasiloxane, Cyclohexasiloxane, Betaine, Glyceryl Stearate, PEG-100 Stearate, Sorbitan Stearate, 1,2-Hexanediol, Stearic Acid, Caprylyl Glycol, Tromethamine, Acrylates/C10-30 Alkyl Acrylate Crosspolymer, Dimethicone/PEG-10/15 Crosspolymer, Aloe Barbadensis Leaf Extract, Sodium Acrylate/Sodium Acryloyldimethyl Taurate Copolymer, Allantoin, Centella Asiatica Extract, Isohexandecane, Dipotassium Glycyrrhizate, Hydrogenated Plyisobutene, Adenosine, Ethlyhexyglycerin, Lavandula Angustifolia (Lavender) Flower Extract, Rosmarinus Officinalis (Rosemary) Leaf Extract, Origanum Vulgare Extract, Thymus Vulgaris (Thyme) Flower/Leaf/Stem Extract, Polysorbate 80, pentylene Glycol, Aspalathus Linearis Extract, Glycrrrhiza Glabra (Licorice) Root Extract, Commiphora Myrrha Resin Extract, Perilla Frutescens Leaf Extract, Yucca Schidigera Root Extract, Anemarrhena Asphodeloides Root Extract, Nicotinoyl Tripeptide-1, Palmitoyl Pentapeptide-4, Caffeoyl sh-Octapeptide-4, Caffeoyl Tripeptide-1,sh-Octapeptide-4, sh-Decapeptide-9, sh-Pentapeptide-19, Sorbitan Oleate, Fragrance (Butylphenyl Methylpropional, Linalool, Benzyl Benzoate, Hexyl Cinnamal, Limonene, Alpha-Isomethyl Ionone)

PURPOSE

With seven peptide in eye cream user can feel a pleasant change by energizing your tired skin. It helps skin elasticity with volufiline content.

keep out of reach of the children

INDICATIONS AND USAGE

Take an appropriate amount of this product and spread it evenly on the skin.

WARNINGS

If there are any abnormal symptoms or side effects such as red spots, swelling, or itching due to direct sunlight during or after using cosmetics. 2. Avoid using areas with wounds. 3. Precautions for storage and handling. 3.1) Keep out reach of children. 3.2) Keep it out of direct sunlight.

DOSAGE AND ADMINISTRATION

for external use only